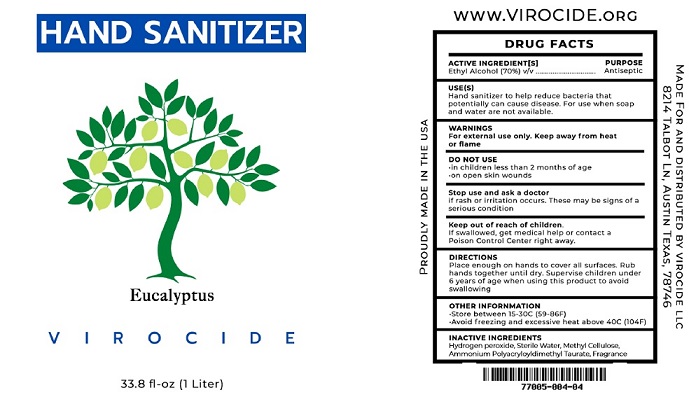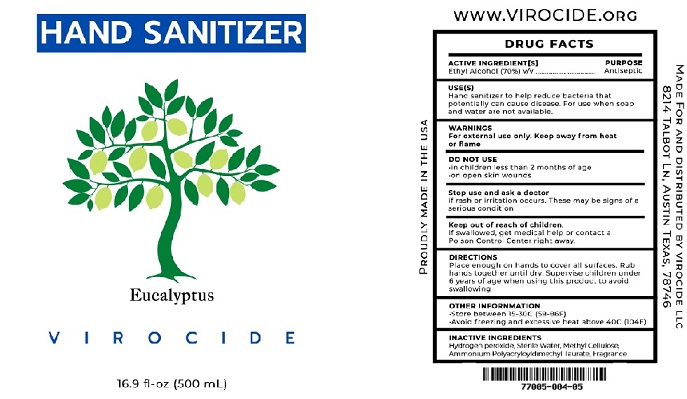 DRUG LABEL: VIROCIDE Hand Sanitizer Eucalyptus
NDC: 77005-004 | Form: GEL
Manufacturer: Virocide LLC
Category: otc | Type: HUMAN OTC DRUG LABEL
Date: 20200911

ACTIVE INGREDIENTS: ALCOHOL 70 L/100 L
INACTIVE INGREDIENTS: HYDROGEN PEROXIDE; WATER; METHYLCELLULOSE, UNSPECIFIED; AMMONIUM POLYACRYLOYLDIMETHYL TAURATE (55000 MPA.S)

DRUG FACTS

ACTIVE INGREDIENT[S]
Ethyl Alcohol (70%) v/v

PURPOSE
Antiseptic

INDICATIONS AND USAGE

USE(S)
Hand sanitizer to help reduce bacteria that
potentially can cause disease. For use when soap
and water are not available.

WARNINGS

WARNINCS
For external use only. Keep away from heat
or flame

DO NOT USE
·in children less than 2 months of age
·on open skin wounds

Stop use and ask a doctor
if rash or irritation occurs. These may be signs of a
serious condition

Keep out of reach of children.
If swallowed. get medical help or contact a
Poison Control Center right away.

DIRECTIONS
Place enough on hands to cover all surfaces. Rub
hands together until dry. Supervise children under
6 years of age when using this product to avoid
swallowing

OTHER INFORNMATION
·Store between 15-30C (59-86F)
·Avoid freezing and excessive heat above 40C (104F)

INACTIVE INGREDIENTS
Hydrogen peroxide, Sterile Water, Methyl Cellulose,
Ammonium Polyacryloyldimethyl Taurate, Fragrance

PACKAGE LABEL

HAND SANITIZER

Eucalyptus
V I R O C I D E

33.8 fl-oz (1 Liter)

www.VIROCIDE.ORG

MADE FOR AND DISTRIBUTED BY VIROCIDE LLC

8214 TALBOT LN, AUSTIN, TEXAS, 78746

77005-004-04

res9.11.20